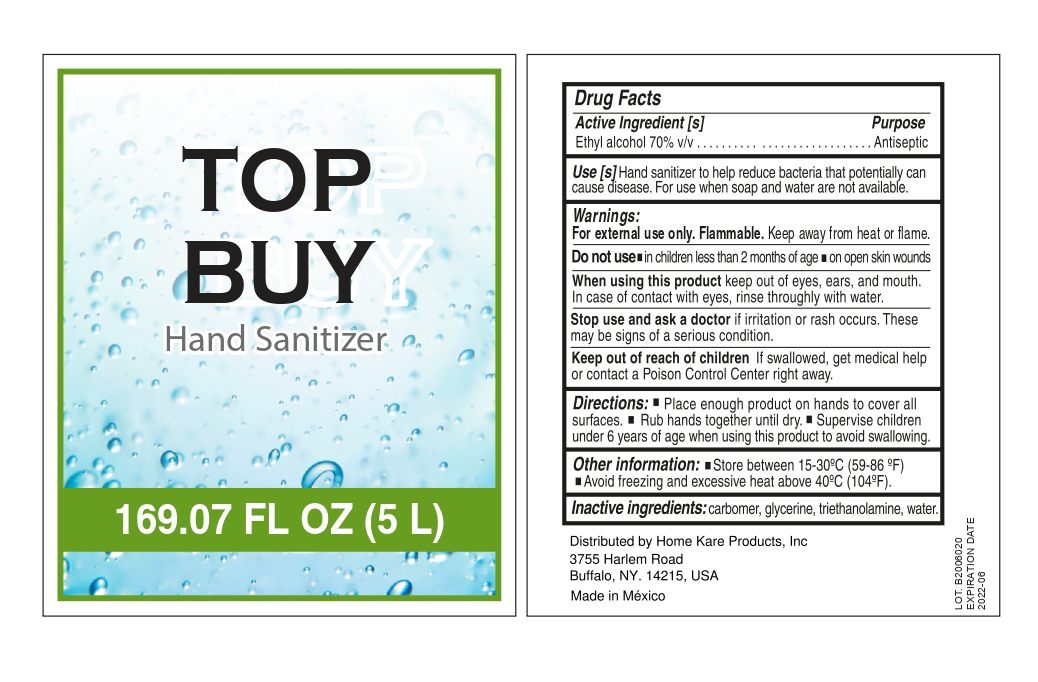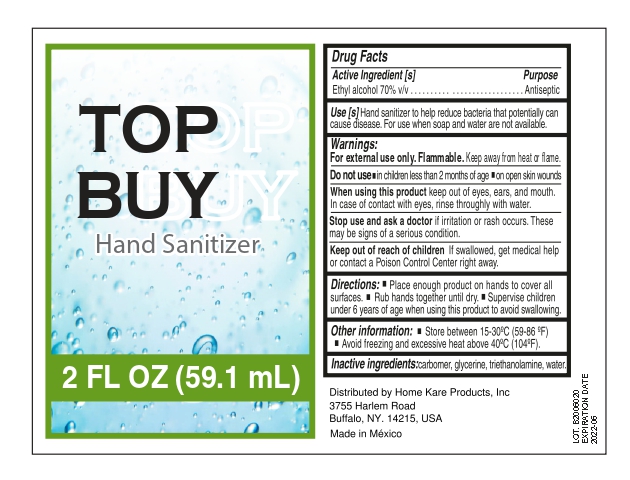 DRUG LABEL: Top Buy Hand Sanitizer
NDC: 79879-002 | Form: GEL
Manufacturer: Ig International Business Group, S.A. de C.V.
Category: otc | Type: HUMAN OTC DRUG LABEL
Date: 20200821

ACTIVE INGREDIENTS: ALCOHOL 70 mL/100 mL
INACTIVE INGREDIENTS: GLYCERIN 0.5 mL/100 mL; CARBOMER 940 0.4 mL/100 mL; WATER 28.6 mL/100 mL; TROLAMINE 0.5 mL/100 mL

79879-002
Hand Sanitizer 70%

Active Ingredient(s)

Alcohol 75% v/v. Purpose: Antiseptic

Purpose

Antiseptic, Hand Sanitizer

Use

Hand Sanitizer to help reduce bacteria that potentially can cause disease. For use when soap and water are not available.

Warnings

For external use only. Flammable. Keep away from heat or flame

Do not use

- in children less than 2 months of age
- on open skin wounds

When using this product keep out of eyes, ears, and mouth. In case of contact with eyes, rinse eyes thoroughly with water.
Stop use and ask a doctor if irritation or rash occurs. These may be signs of a serious condition.
Keep out of reach of children. If swallowed, get medical help or contact a Poison Control Center right away.

Stop use and ask a doctor if irritation or rash occurs. These may be signs of a serious condition.

Keep out of reach of children. If swallowed, get medical help or contact a Poison Control Center right away.

Directions

- Place enough product on hands to cover all surfaces. Rub hands together until dry.
- Supervise children under 6 years of age when using this product to avoid swallowing.

Other information

- Store between 15-30C (59-86F)
- Avoid freezing and excessive heat above 40C (104F)

Inactive ingredients

water, glycerin, triethanolamine, carbomer 940

Package Label - Principal Display Panel

60 mL NDC:79879-001-01

5,000 mL NDC:79879-001-02